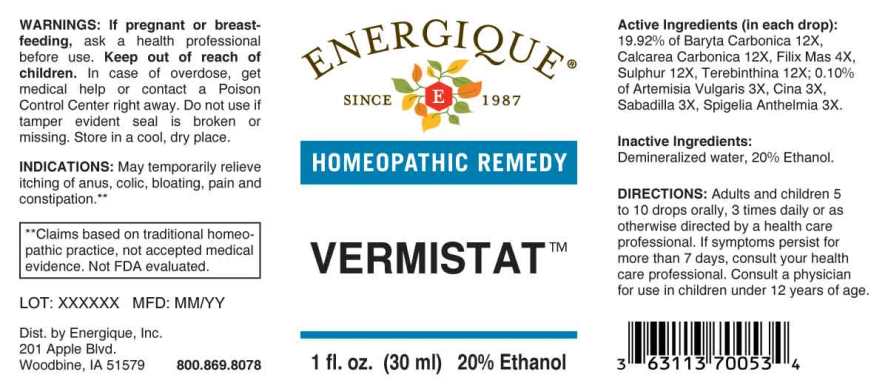 DRUG LABEL: Vermistat
NDC: 44911-0612 | Form: LIQUID
Manufacturer: Energique, Inc.
Category: homeopathic | Type: HUMAN OTC DRUG LABEL
Date: 20231102

ACTIVE INGREDIENTS: ARTEMISIA VULGARIS ROOT 3 [hp_X]/1 mL; ARTEMISIA CINA PRE-FLOWERING TOP 3 [hp_X]/1 mL; SCHOENOCAULON OFFICINALE SEED 3 [hp_X]/1 mL; SPIGELIA ANTHELMIA 3 [hp_X]/1 mL; DRYOPTERIS FILIX-MAS ROOT 4 [hp_X]/1 mL; BARIUM CARBONATE 12 [hp_X]/1 mL; OYSTER SHELL CALCIUM CARBONATE, CRUDE 12 [hp_X]/1 mL; SULFUR 12 [hp_X]/1 mL; TURPENTINE OIL 12 [hp_X]/1 mL
INACTIVE INGREDIENTS: WATER; ALCOHOL

Drug Facts:

ACTIVE INGREDIENTS:

(in each drop): 19.92% of Baryta Carbonica 12X, Calcarea Carbonica 12X, Filix Mas 4X, Sulphur 12X, Terebinthina 12X; 0.10% of Artemisia Vulgaris 3X, Cina 3X, Sabadilla 3X, Spigelia Anthelmia 3X.

INDICATIONS:

May temporarily relieve itching of anus, colic, bloating, pain and constipation.**

**Claims based on traditional homeopathic practice, not accepted medical evidence. Not FDA evaluated.

WARNINGS:

If pregnant or breast-feeding, ask a health professional before use.

Keep out of reach of children. In case of overdose, get medical help or contact a Poison Control Center right away.

Do not use if tamper evident seal is broken or missing.

Store in a cool, dry place.

Keep out of reach of children. In case of overdose, get medical help or contact a Poison Control Center right away.

DIRECTIONS:

Adults and children 5 to 10 drops orally, 3 times daily or as otherwise directed by a health care professional. If symptoms persist for more than 7 days, consult your health care professional. Consult a physician for use in children under 12 years of age.

INDICATIONS:

May temporarily relieve itching of anus, colic, bloating, pain and constipation.**

**Claims based on traditional homeopathic practice, not accepted medical evidence. Not FDA evaluated.

INACTIVE INGREDIENTS:

Demineralized water, 20% Ethanol.

QUESTIONS:

Dist. by Energique, Inc.

201 Apple Blvd

Woodbine, IA 51579 800.869.8078

PACKAGE LABEL DISPLAY:

ENERGIQUE

SINCE 1987

HOMEOPATHIC REMEDY

VERMISTAT

1 fl. oz. (30 ml)